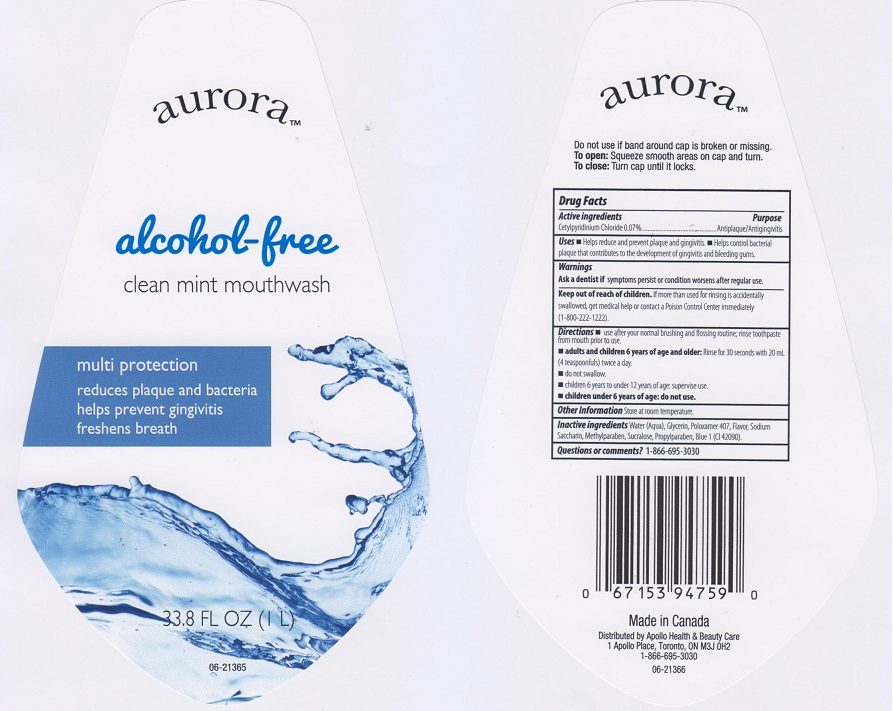 DRUG LABEL: Aurora Alcohol Free Clean Mint
NDC: 63148-553 | Form: MOUTHWASH
Manufacturer: Apollo Health and Beauty Care
Category: otc | Type: HUMAN OTC DRUG LABEL
Date: 20160615

ACTIVE INGREDIENTS: CETYLPYRIDINIUM CHLORIDE 0.7 mg/1 mL
INACTIVE INGREDIENTS: WATER; GLYCERIN; POLOXAMER 407; SACCHARIN SODIUM; METHYLPARABEN; SUCRALOSE; PROPYLPARABEN; FD&C BLUE NO. 1

DRUG FACTS

Active ingredient

Cetylpyridinium Chloride 0.07%

Purpose

Antiplaque/Antigingivitis

Uses

- Helps reduce and prevent plaque and gingivitis.
- Helps control bacteria plaque that contributes to the development of gingivitis and bleeding gums.

Warnings

Ask a dentist if symptoms persist or condition worsens after regular use.

Keep out of reach of children.

If more than used for rinsing is accidentally swallowed, get medical help or contact a Poison Control Center immediately (1-800-222-1222).

Directions

- Use after your normal brushing and flossing routein; rinse toothpaste from mouth prior to use.
- Adults and children 6 years of age and older: Rinse for 30 seconds with 20 mL (4 teaspoonfuls) twice a day.
- do not swallow.
- children 6 years to under 12 years of age: supervise use.
- children under 6 years of age: do not use.

Other information

Store at room temperature.

Inactive ingredients

Water (Aqua), Glycerin, Poloxamer 407, Flavor, Sodium Saccharin, Methylparaben, Sucralose, Propylparaben, Blue 1 (CI 42090).

Questions or comments?

1-866-695-3030